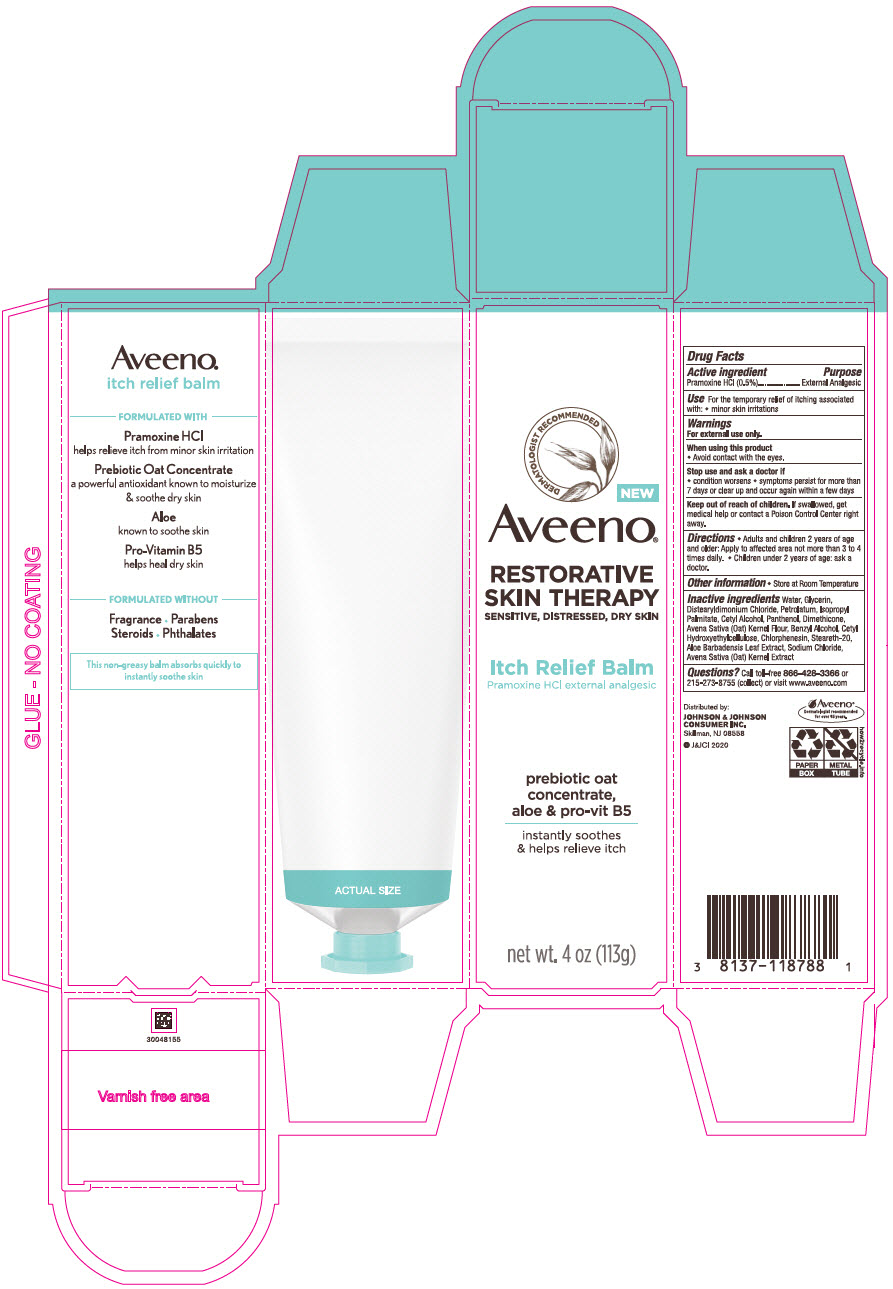 DRUG LABEL: Aveeno Restorative Skin Therapy Itch Relief Balm
NDC: 69968-0637 | Form: CREAM
Manufacturer: Kenvue Brands LLC
Category: otc | Type: HUMAN OTC DRUG LABEL
Date: 20241105

ACTIVE INGREDIENTS: PRAMOXINE HYDROCHLORIDE 5 mg/1 g
INACTIVE INGREDIENTS: GLYCERIN; DISTEARYLDIMONIUM CHLORIDE; PETROLATUM; ISOPROPYL PALMITATE; WATER; CETYL ALCOHOL; PANTHENOL; DIMETHICONE; OATMEAL; BENZYL ALCOHOL; CHLORPHENESIN; STEARETH-20; ALOE VERA LEAF; SODIUM CHLORIDE; OAT

Aveeno® RESTORATIVE SKIN THERAPY Itch Relief Balm

Drug Facts

Active Ingredient

Pramoxine HCl (0.5%)

Purpose

External Analgesic

Use

For the temporary relief of itching associated with:

- minor skin irritations

Warnings

For external use only.

When using this product

- Avoid contact with the eyes.

Stop use and ask a doctor if

- condition worsens
- symptoms persist for more than 7 days or clear up and occur again within a few days

Keep out of reach of children. If swallowed, get medical help or contact a Poison Control Center right away.

Directions

- Adults and children 2 years of age and older: Apply to affected area not more than 3 to 4 times daily.
- Children under 2 years of age: ask a doctor.

Other Information

Store at Room Temperature

Inactive Ingredients

Water, Glycerin, Distearyldimonium Chloride, Petrolatum, Isopropyl Palmitate, Cetyl Alcohol, Panthenol, Dimethicone, Avena Sativa (Oat) Kernel Flour, Benzyl Alcohol, Cetyl Hydroxyethylcellulose, Chlorphenesin, Steareth-20, Aloe Barbadensis Leaf Extract, Sodium Chloride, Avena Sativa (Oat) Kernel Extract

Questions?

Call toll-free 866-428-3366 or 215-273-8755 (collect) or visit www.aveeno.com

Distributed by:
JOHNSON & JOHNSON
CONSUMER INC.
Skillman, NJ 08558

PRINCIPAL DISPLAY PANEL - 113 g Tube Carton

DERMATOLOGIST RECOMMENDED
NEW
Aveeno®
RESTORATIVE
SKIN THERAPY
SENSITIVE, DISTRESSED, DRY SKIN
Itch Relief Balm
Pramoxine HCL external analgesic
prebiotic oat
concentrate,
aloe & pro-vit B5
instantly soothes
& helps relieve itch
net wt. 4 oz (113g)